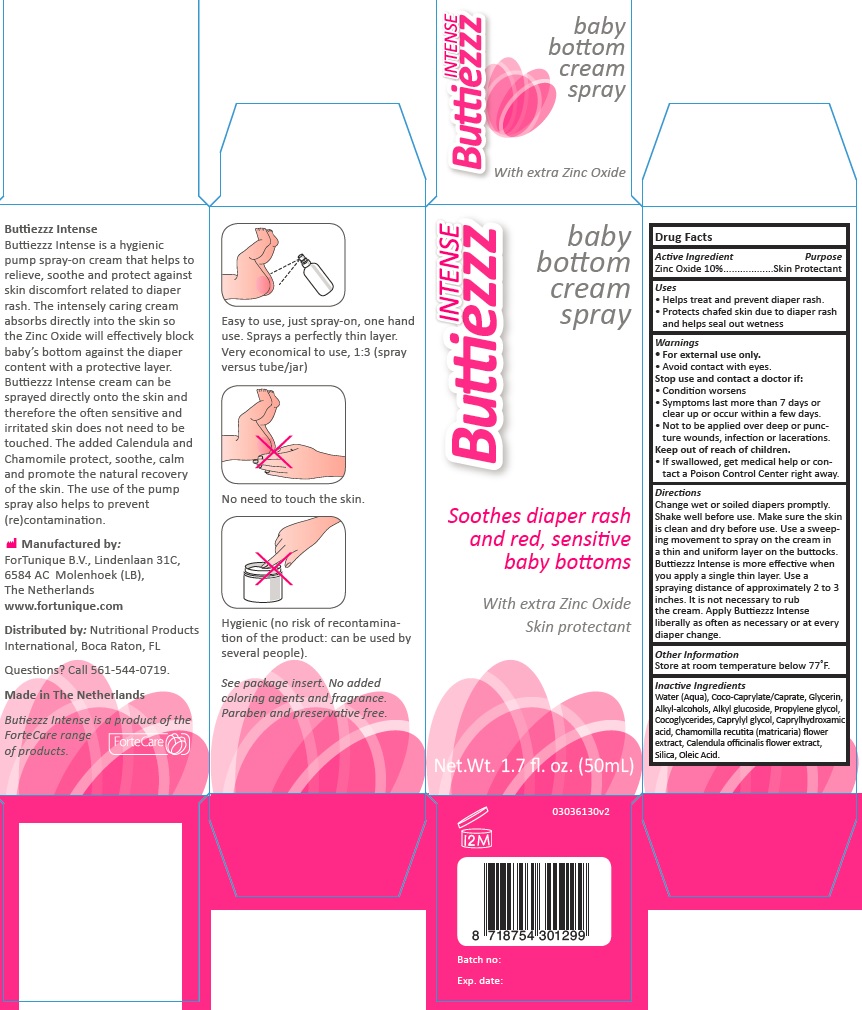 DRUG LABEL: Buttiezzz Intense
NDC: 70359-4102 | Form: SPRAY
Manufacturer: Fortunique B.V.
Category: otc | Type: HUMAN OTC DRUG LABEL
Date: 20161214

ACTIVE INGREDIENTS: ZINC OXIDE 10 g/100 g
INACTIVE INGREDIENTS: CAPRYLHYDROXAMIC ACID; CALENDULA OFFICINALIS FLOWER; COCO-GLYCERIDES; PROPYLENE GLYCOL; SILICON DIOXIDE; OLEIC ACID; CAPRYLYL GLYCOL; CHAMOMILE; COCO-CAPRYLATE/CAPRATE; GLYCERIN; C14-22 ALCOHOLS; C12-20 ALKYL GLUCOSIDE; WATER

Active Ingredients

Zinc Oxide 10%

Purpose

Skin Protectant

Uses

Helps treat and prevent diaper rash

Protect chafed skin due to diaper rash and helps seal out wetness

Warning

For external use only

Avoid contact with eyes

Stop use and contact a Doctor if

Condition worsens

Symptoms last more 7 days or clear up or occur within a few days

Not to be applied over deep or puncture wounds, infection or lacerations

Keep out of reach of children

If swallowed, get medical help or contact a Poison Control Center right away

Directions

Change wet or soiled diapers promptly

Shake well before use. Make sure the thin is clean and dry before use. Use a sweeping movement to spray on the cream in a thin and uniform layer on the buttocks

Buttiezzz Intense is more effective when you apply a single thin layer. Use a spraying distance approximately 2 to 3 inches. It is not necessary to rub the cream. Apply Butiezzz Intense liberally as often as necessary or at every diaper change

Other Information

Store at room temperature bellow 77º F

Inactive Ingredients

Water(aqua)

Coco-Caprilate/Caprate

Glycerin

Alkyl-Alcohols

Alkyl Glucoside

Propilene Glycol

Cocoglycerides

Caprylyl glycol

Capryl Hydroxamic acid

Chamomilla Recutita(Matricaria)Flower Extract

Calendula Officinalis Flower Extract

Silica

Oleic Acid